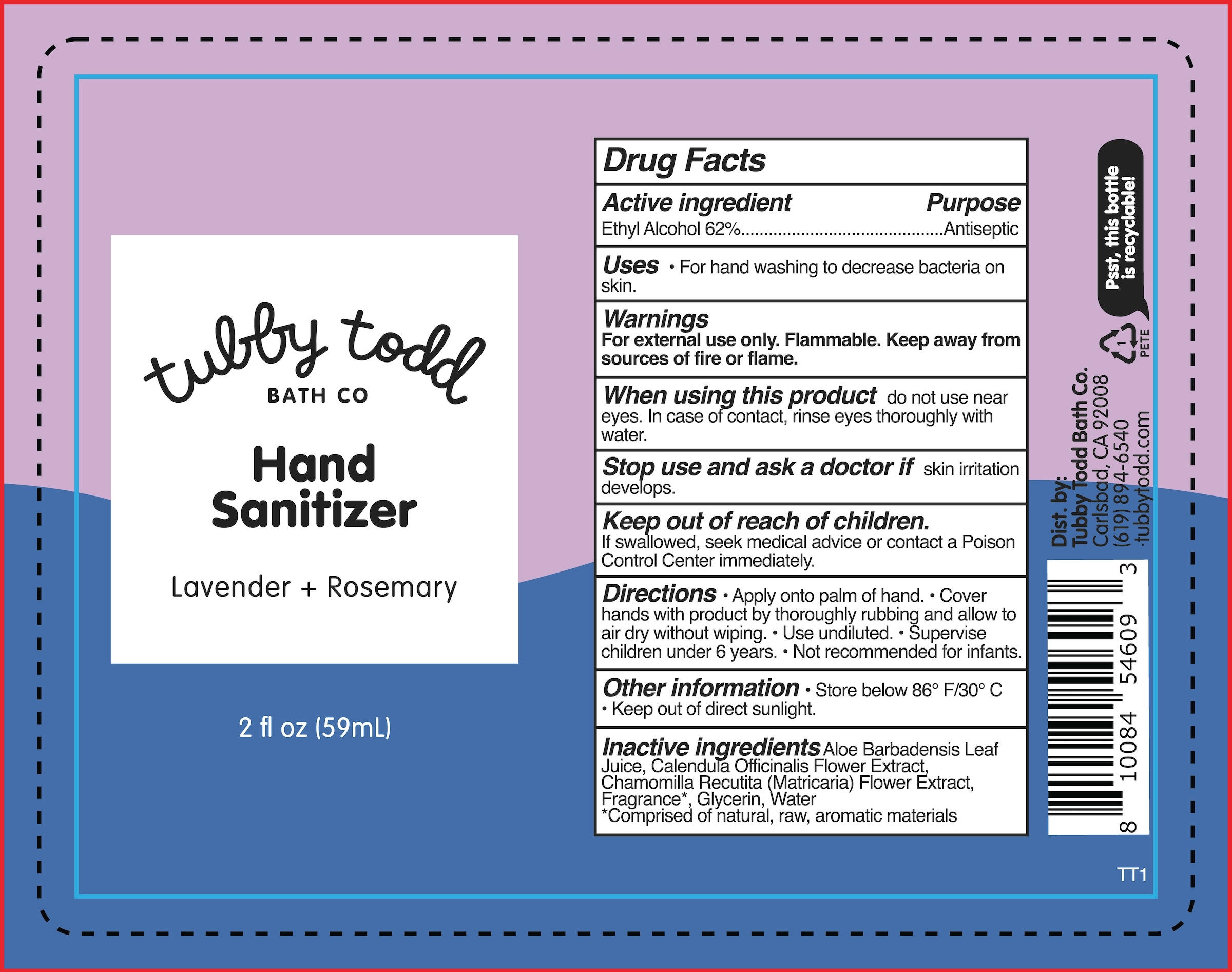 DRUG LABEL: Hand Sanitizer (Lavender Rosemary)
NDC: 73088-205 | Form: SPRAY
Manufacturer: Tubby Todd
Category: otc | Type: HUMAN OTC DRUG LABEL
Date: 20241218

ACTIVE INGREDIENTS: ALCOHOL 62 mL/100 mL
INACTIVE INGREDIENTS: CALENDULA OFFICINALIS FLOWER; WATER; ALOE BARBADENSIS LEAF JUICE; GLYCERIN; CHAMOMILE

Active ingredients

Ethyl Alcohol 62%

Purpose

Antiseptic

Uses

• For hand washing to decrease bacteria on skin.

Warnings

For external use only.

Flammable.
Keep away from sources of fire or flame

When using this product

do not use near eyes. In case of contact, rinse eyes thoroughly with water.

Stop and ask a doctor if

skin irritation develops.

Keep out of reach of children.

If swallowed, seek medical advice or contact a Poison Control Center immediately.

Directions

Apply onto palm of hand
Cover hands with product by thoroughly rubbing and allow to air dry without wiping
Use undiluted
Supervise children under 6 years.
Not recommended for infants

Other information

Store below 86° F/30° C
Keep out of direct sunlight

Inactive ingredients

Aloe Barbadensis Leaf Juice, Calendula Officinalis Flower Extract, Chamomilla Recutita (Matricaria) Flower Extract, Fragrance*, Glycerin, Water
*Comprised of natural, raw, aromatic materials